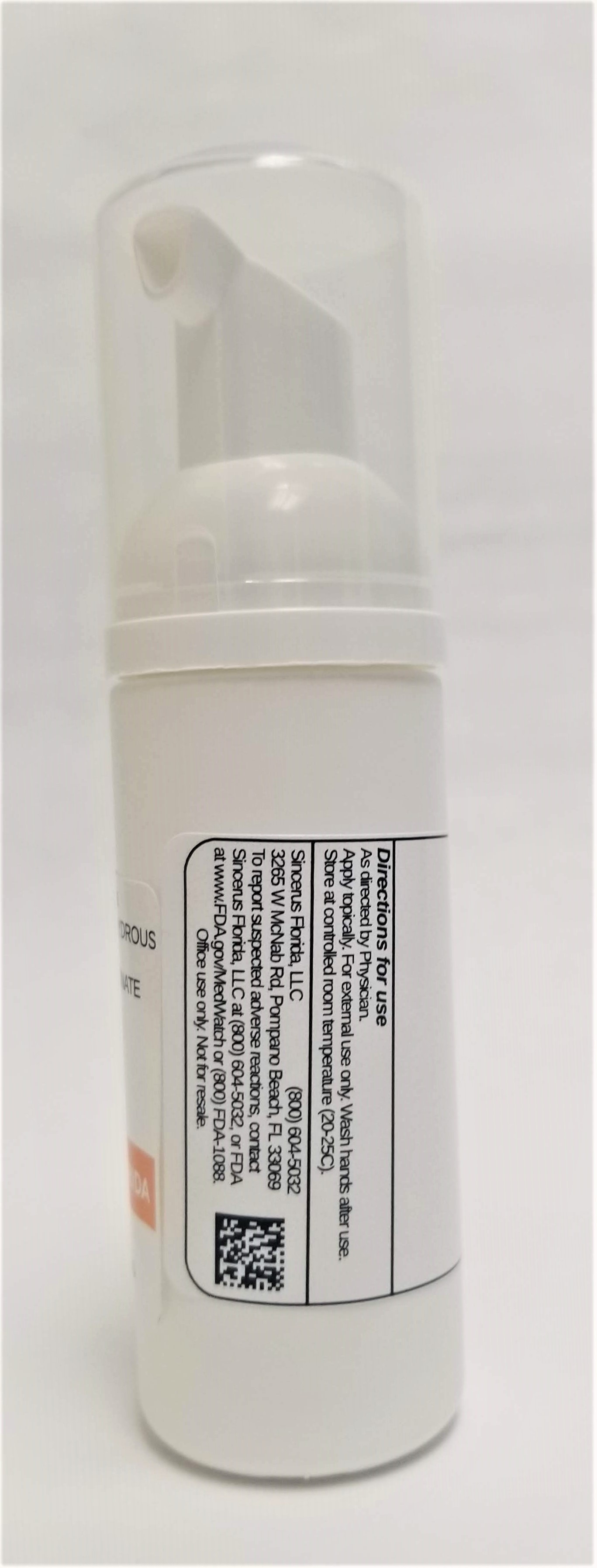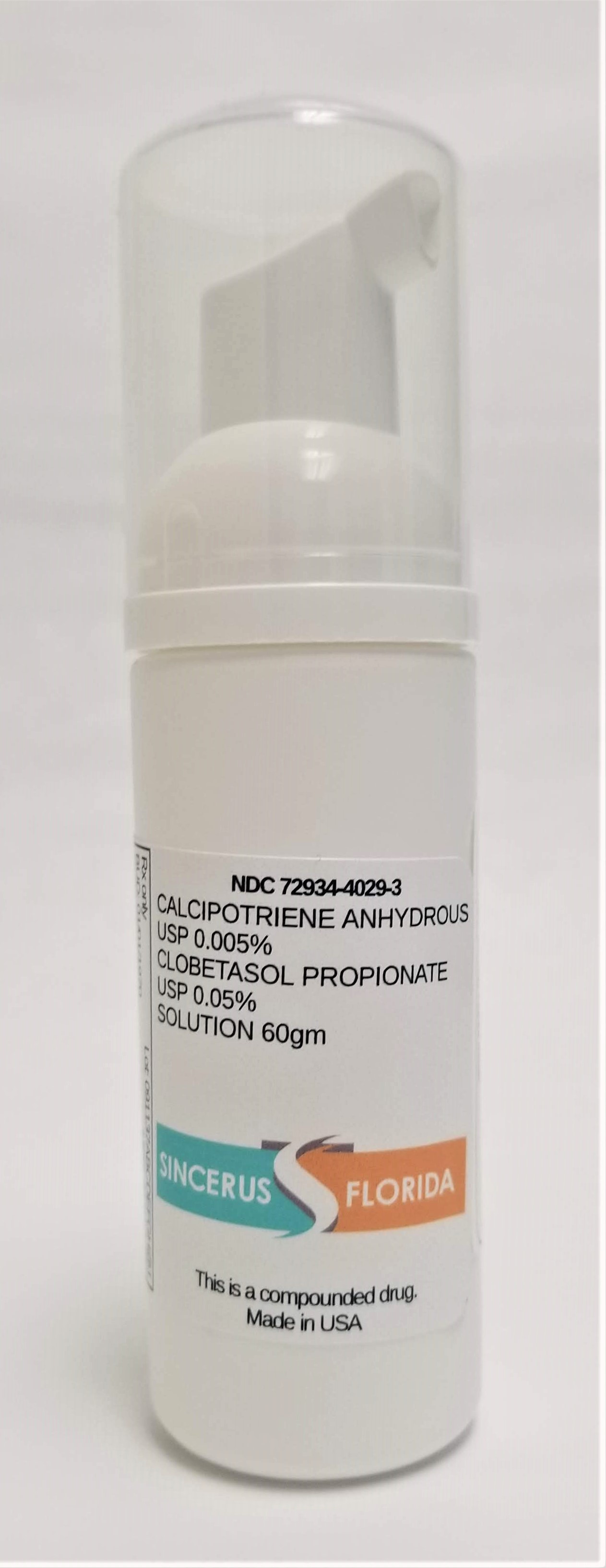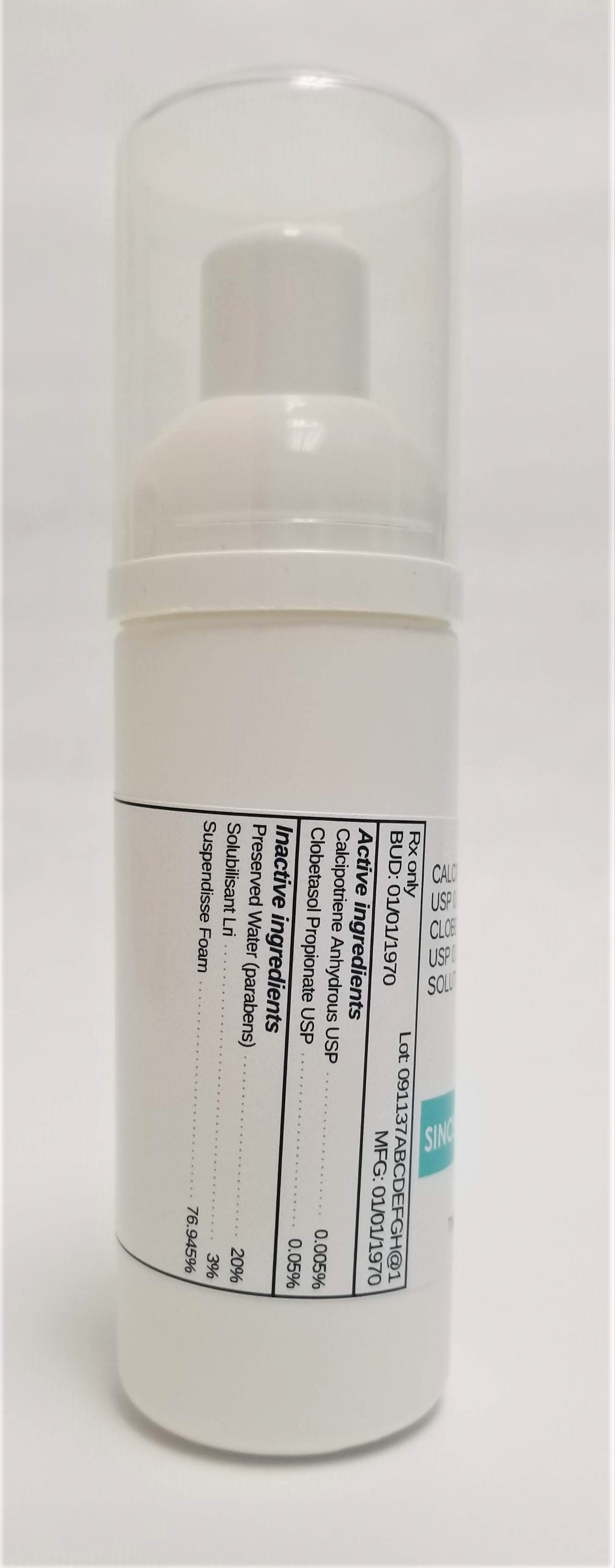 DRUG LABEL: CALCIPOTRIENE 0.005% / CLOBETASOL PROPIONATE 0.05%
NDC: 72934-4029 | Form: SOLUTION
Manufacturer: Sincerus Florida, LLC
Category: prescription | Type: HUMAN PRESCRIPTION DRUG LABEL
Date: 20190520

ACTIVE INGREDIENTS: CALCIPOTRIENE 0.005 g/100 g; CLOBETASOL PROPIONATE 0.05 g/100 g

CALCIPOTRIENE 0.005% / CLOBETASOL PROPIONATE 0.05%